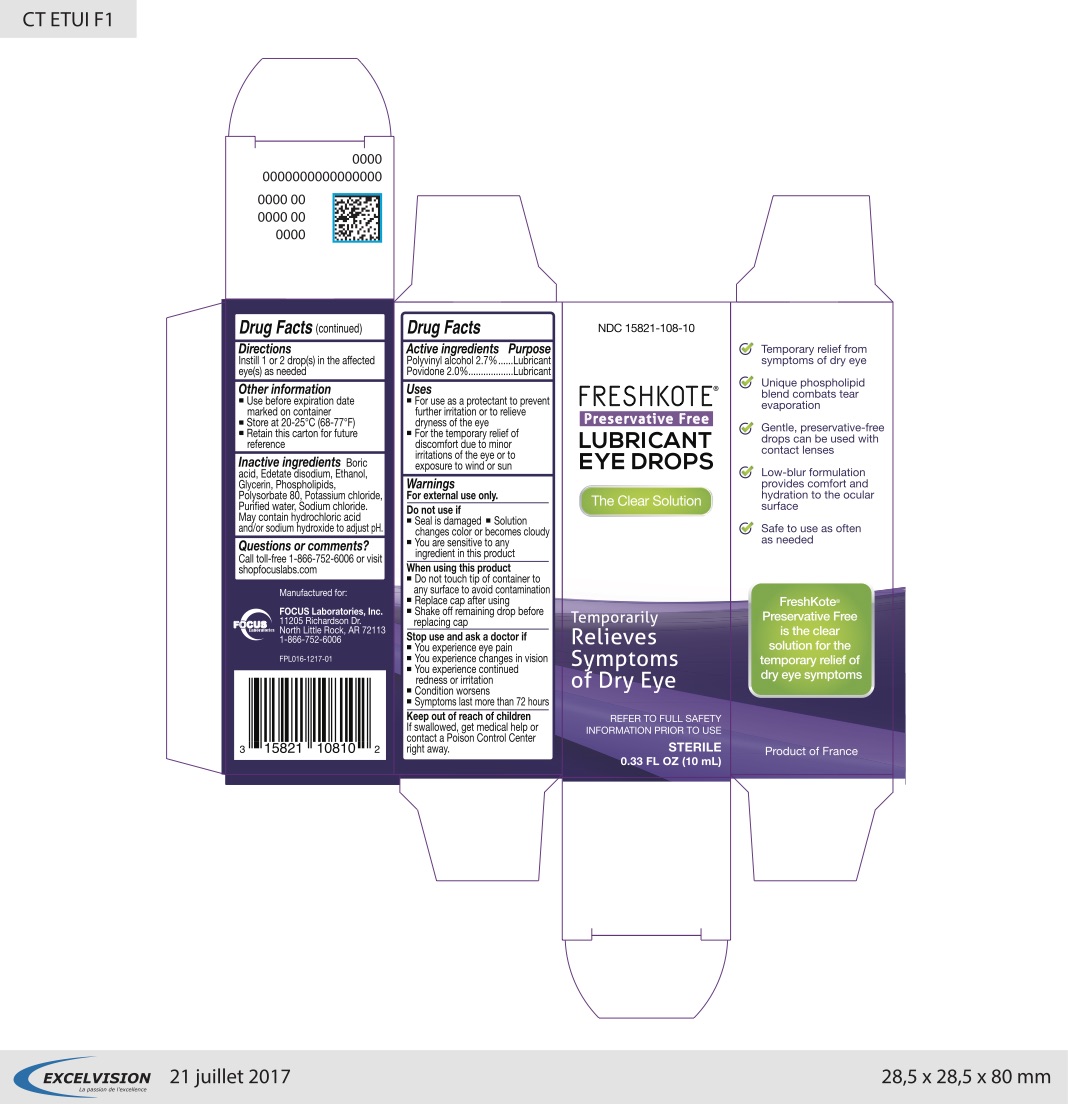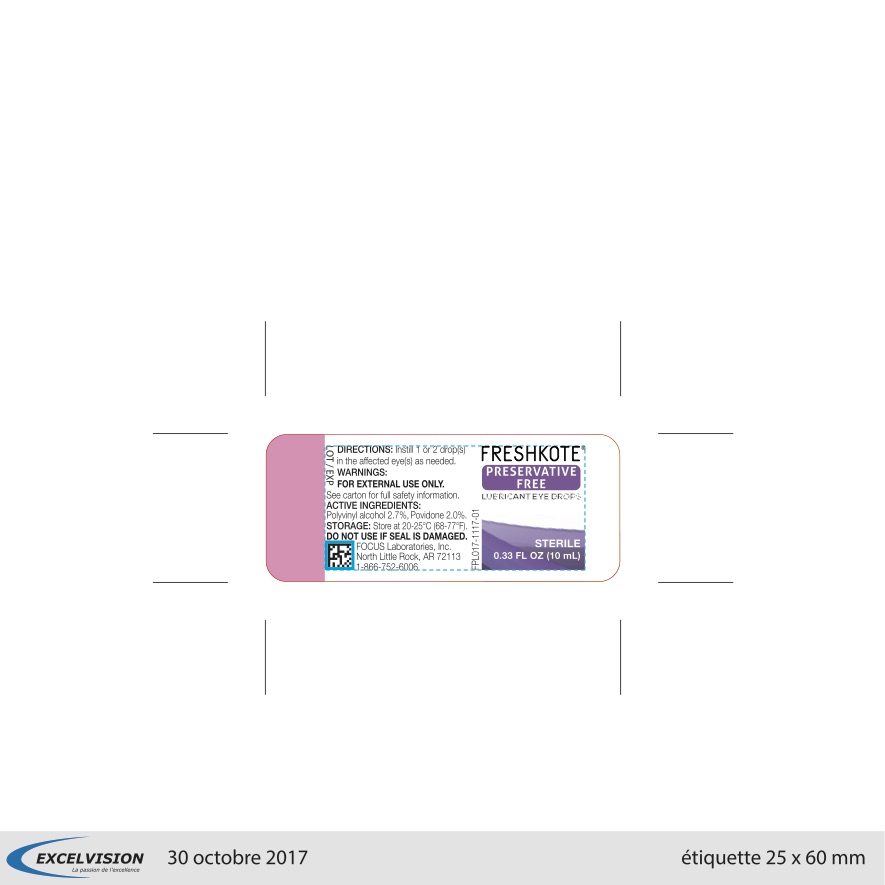 DRUG LABEL: FreshKote Preservative Free Lubricating Eye Drops
NDC: 15821-108 | Form: SOLUTION
Manufacturer: FOCUS Laboratories, Inc.
Category: otc | Type: HUMAN OTC DRUG LABEL
Date: 20180725

ACTIVE INGREDIENTS: POVIDONE 20 g/1000 mL; POLYVINYL ALCOHOL, UNSPECIFIED 27 g/1000 mL
INACTIVE INGREDIENTS: BORIC ACID; EDETATE DISODIUM; ALCOHOL; GLYCERIN; EGG PHOSPHOLIPIDS; POLYSORBATE 80; POTASSIUM CHLORIDE; SODIUM CHLORIDE; WATER

FreshKote Preservative Free Lubricating Eye Drops

Active Ingredients Purpose

Polyvinyl Alcohol 2.7%.........Lubricant

Povidone 2.0%....................Lubricant

Uses

- For the temporary relief of discomfort due to minor irritations of the eye or to exposure to wind or sun

Warnings

For external use only.

Do not use if

- Seal is damaged
- Solution changes color or becomes cloudy
- You are sensitive to any ingredient in this product

Stop use and ask a doctor if

- You experience eye pain
- You experience changes in vision
- You experience continued redness or irritation
- Condition worsens
- Symptoms last more than 72 hours

Keep out of reach of children

If swallowed, get medical help or contact a Poison Control Center right away.

Directions

Instill 1 or 2 drop(s) in the affected eye(s) as needed

Other information

- Use before expiration date marked on container
- Store at 20-25οC(68-77οF)
- Retain this carton for future reference

Inactive ingredients

Boric acid, Edetate disodium, Ethanol, Glycerin, Phospholipids, Polysorbate 80, Potassium chloride, Purified water, Sodium chloride. May contain hydrochloric acid and/or sodium hydroxide to adjust pH.

PURPOSE

For the temporary relief of discomfort due to minor irritations of the eye or to exposure to wind or sun